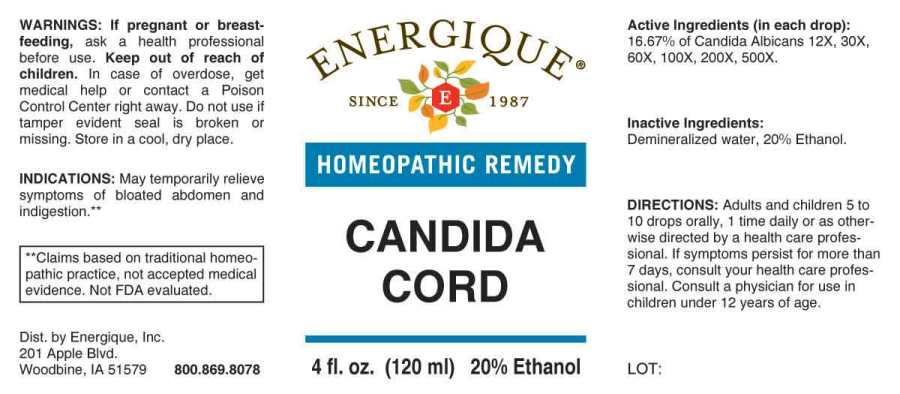 DRUG LABEL: Candida Cord
NDC: 44911-0656 | Form: LIQUID
Manufacturer: Energique, Inc.
Category: homeopathic | Type: HUMAN OTC DRUG LABEL
Date: 20240712

ACTIVE INGREDIENTS: CANDIDA ALBICANS 12 [hp_X]/1 mL
INACTIVE INGREDIENTS: WATER; ALCOHOL

DRUG FACTS:

ACTIVE INGREDIENTS:

(in each drop): 16.67% of Candida Albicans 12X, 30X, 60X, 100X, 200X, 500X.

INDICATIONS:

May temporarily relieve symptoms of bloated abdomen and indigestion**

**Claims based on traditional homeopathic practice, not accepted medical evidence. Not FDA evaluated.

WARNINGS:

If pregnant or breast-feeding, ask a health professional before use.

Keep out of reach of children. In case of overdose, get medical help or contact a Poison Control Center right away.

Do not use if tamper evident seal is broken or missing.

Store in cool, dry place.

KEEP OUT OF REACH OF CHILDREN.

In case of overdose, get medical help or contact a Poison Control Center right away.

DIRECTIONS:

Adults and children 5 to 10 drops orally, 1 time daily or as otherwise directed by a health care professional. If symptoms persist for more than 7 days, consult your health care professional. Consult a physician for use in children under 12 years of age.

INDICATIONS:

May temporarily relieve symptoms of bloated abdomen and indigestion**

**Claims based on traditional homeopathic practice, not accepted medical evidence. Not FDA evaluated.

INACTIVE INGREDIENTS:

Demineralized Water, Energized Water, 20% Ethanol.

QUESTIONS:

Dist. By Energique, Inc.

201 Apple Blvd.

Woodbine, IA 51579 800.869.8078

PACKAGE LABEL DISPLAY:

ENERGIQUE

SINCE 1987

HOMEOPATHIC REMEDY

CANDIDA CORD

4 fl. oz. (120ml)